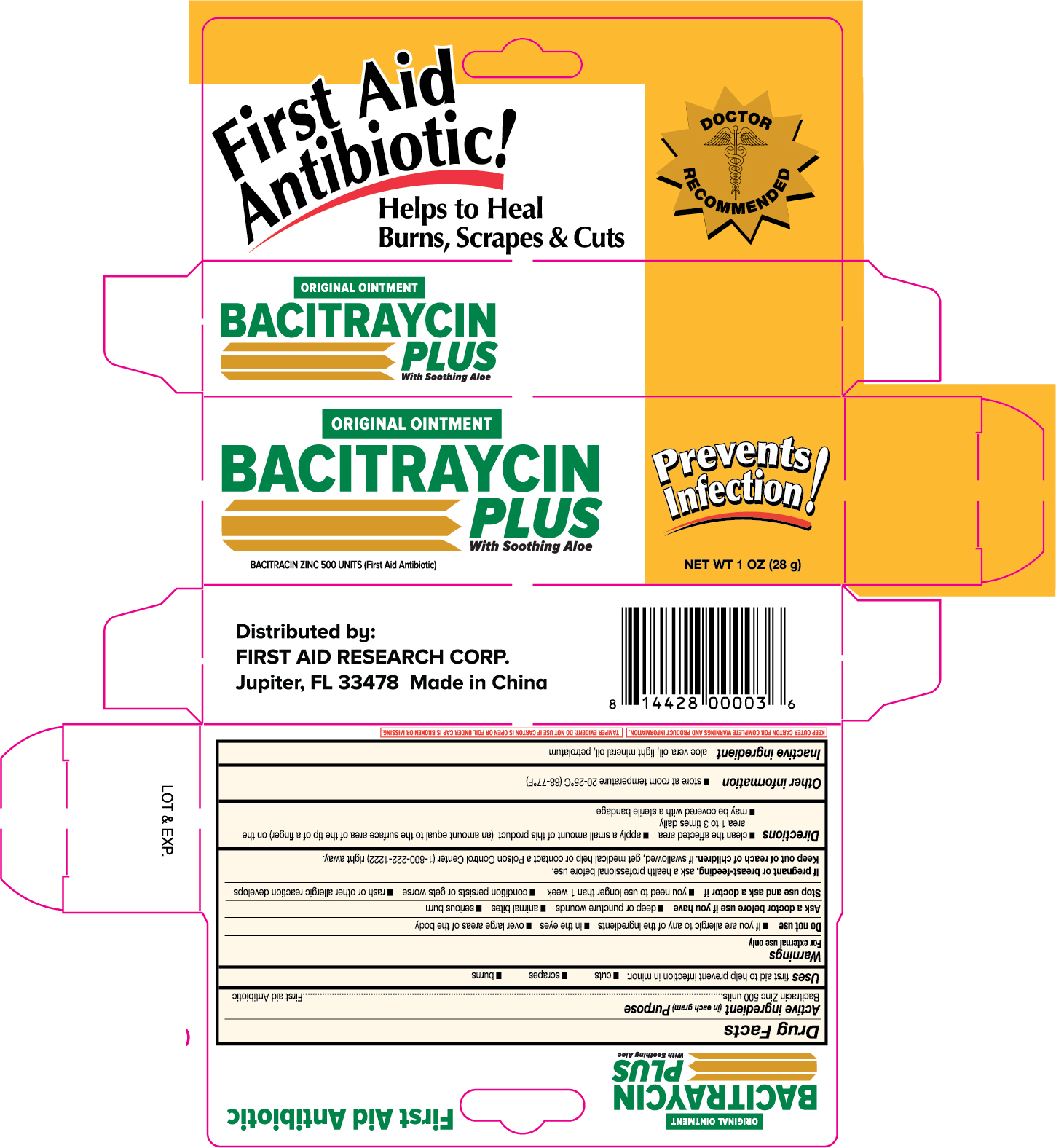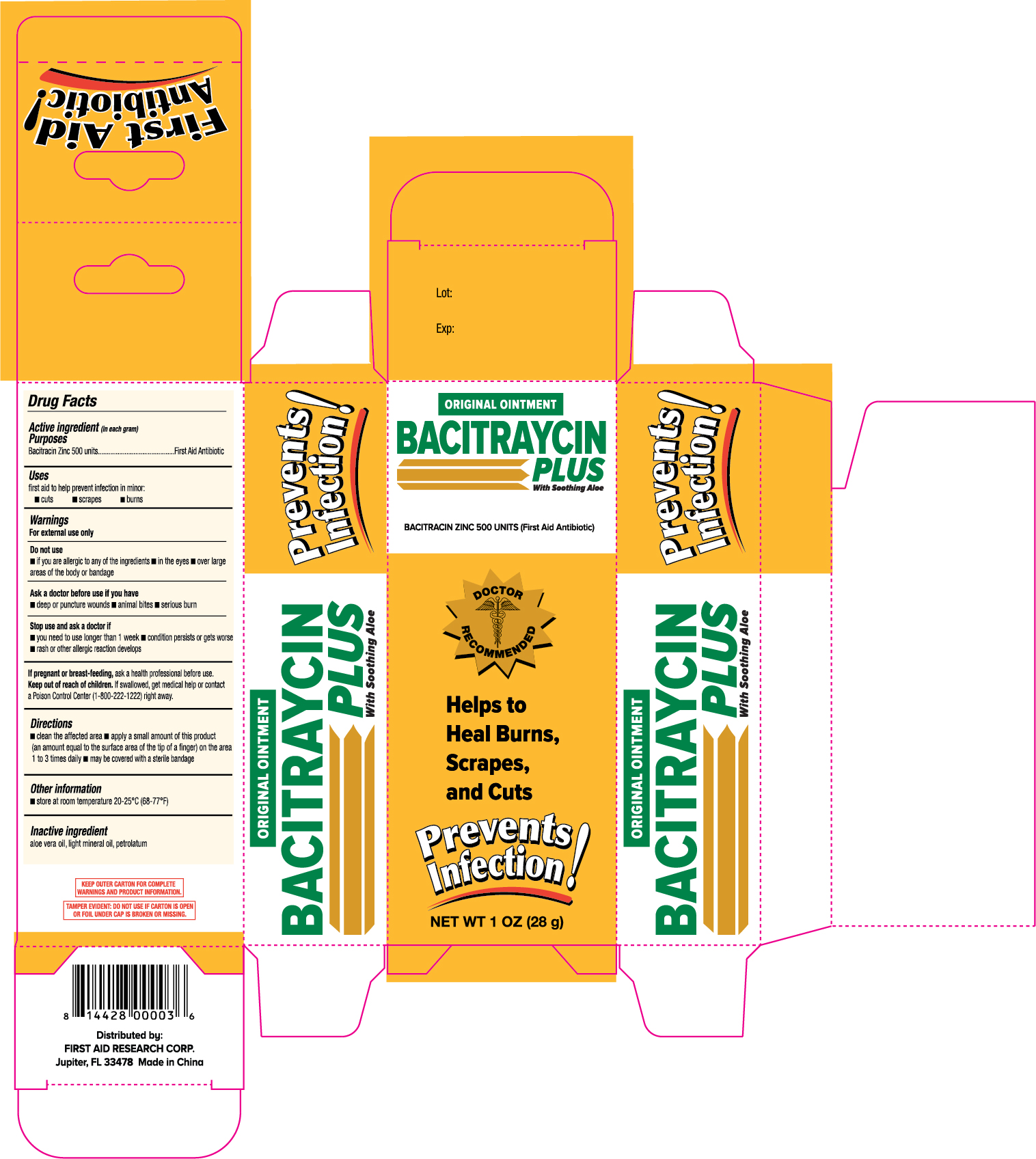 DRUG LABEL: First Aid Antibiotic Bacitracin with Zinc
NDC: 75983-001 | Form: OINTMENT
Manufacturer: First Aid Research Corp.
Category: otc | Type: HUMAN OTC DRUG LABEL
Date: 20201028

ACTIVE INGREDIENTS: BACITRACIN ZINC 500 [USP'U]/1 g
INACTIVE INGREDIENTS: LIGHT MINERAL OIL; ALOE VERA LEAF; PETROLATUM

First Aid Research Bacitraycin Plus 1oz 49003 & 89770V (2019)

Active ingredient (each gram contains)

Bacitracin zinc 500 units

Purpose

First Aid Antibiotic

Uses

first aid to help prevent infection in

- minor cuts
- scrapes
- burns

Warnings

For external use only.

Do not use

- in the eyes
- over large areas of the body
- if you are allergic to any of the ingredients
- longer than 1 week unless directed by a doctor

Ask a doctor before use in case of deep or puncture wounds, animal bites, or serious burns.

Stop use and ask a doctor if

- the condition persists or gets worse
- a rash or other allergic reaction develops

PREGNANCY OR BREAST FEEDING

If pregnant or breast-feeding, ask a health professional before use.

Keep out of reach of children. If swallowed, get medical help or contact a Poison Control Center (1-800-222-1222) right away.

Directions

- clean the affected area
- apply a small amount of this product (an amount equal to the surface area of the tip of a finger) on the area 1 to 3 times daily
- may be covered with a sterile bandage

Other information

- store at 15° to 25° C (59° to 77° F)

Inactive ingredients

aloe vera gel, light mineral oil and white petrolatum

Distributed by:

FIRST AID RESEARCH CORP.

Jupitor, FL 33478 Made in China